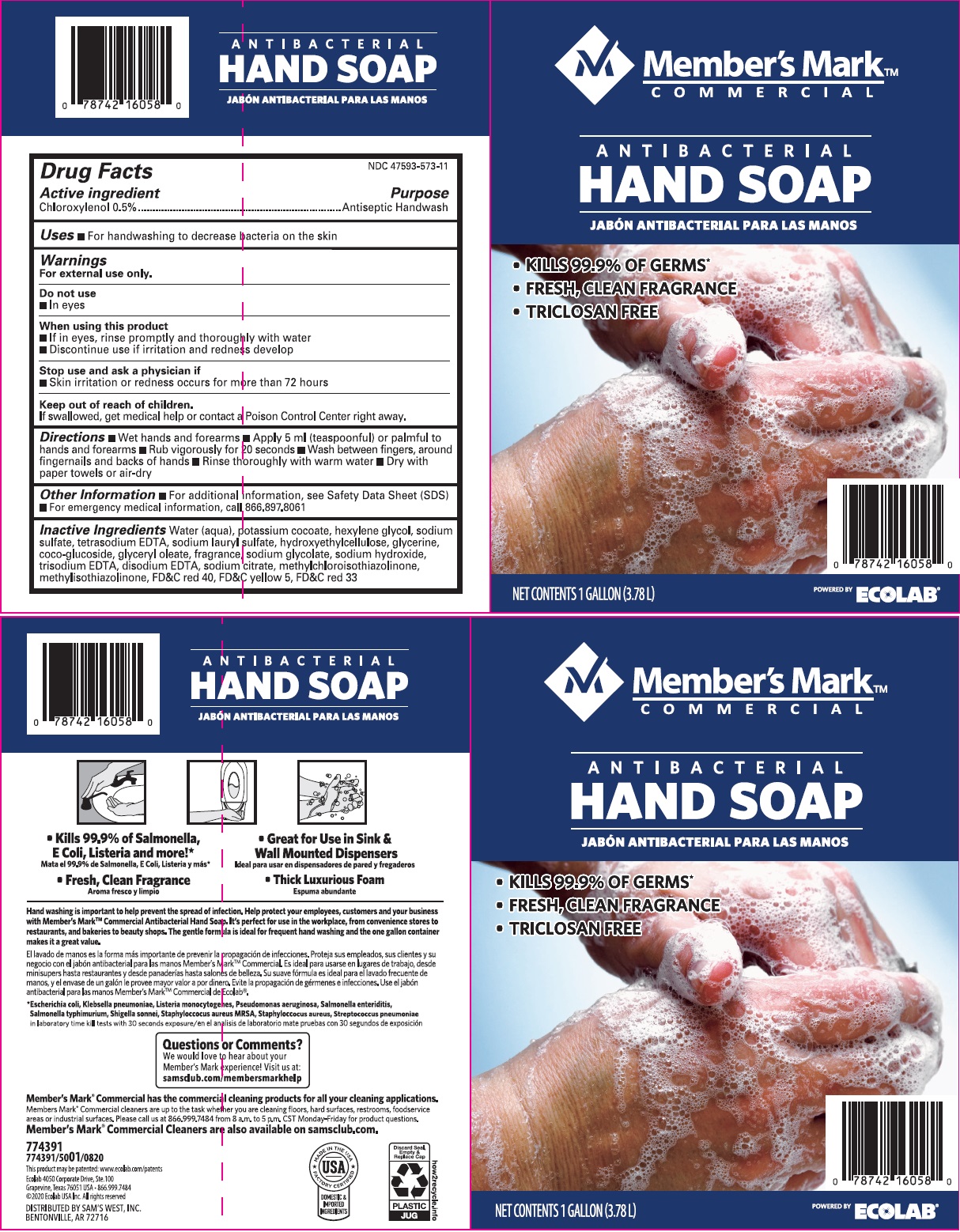 DRUG LABEL: Members Mark
NDC: 47593-573 | Form: SOLUTION
Manufacturer: Ecolab Inc.
Category: otc | Type: HUMAN OTC DRUG LABEL
Date: 20251230

ACTIVE INGREDIENTS: CHLOROXYLENOL 5 mg/1 mL
INACTIVE INGREDIENTS: WATER; POTASSIUM COCOATE; HEXYLENE GLYCOL; SODIUM SULFATE ANHYDROUS; EDETATE SODIUM; SODIUM LAURYL SULFATE; HYDROXYETHYL CELLULOSE (3000 MPA.S AT 1%); GLYCERIN; COCO-GLUCOSIDE; GLYCERYL OLEATE; SODIUM GLYCOLATE; SODIUM HYDROXIDE; EDETATE TRISODIUM; EDETATE DISODIUM; SODIUM CITRATE; METHYLCHLOROISOTHIAZOLINONE; METHYLISOTHIAZOLINONE; FD&C RED NO. 40; FD&C YELLOW NO. 5; D&C RED NO. 33

Drug Facts

Active ingredient

Chloroxylenol 0.5%

Purpose

Antiseptic handwash

Uses

- For handwashing to decrease bacteria on the skin

Warnings

For external use only.

Do not use

- In eyes

When using this product

- If in eyes, rinse promptly and thoroughly with water
- Discontinue use if irritation and redness develop

Stop use and ask a physician if

- Skin irritation or redness occurs for more than 72 hours

Keep out of reach of children.

If swallowed, get medical help or contact a Poison Control Center right away.

Directions

• Wet hands and forearms • Apply 5 ml (teaspoonful) or palmful to hands and forearms • Rub vigorously for 20 seconds • Wash between fingers, around fingernails and backs of hands • Rinse thoroughly with warm water Dry with paper towels or air-dry

Other Information

- For additional information, see Safety Data Sheet (SDS)
- For emergency medical information, call 866.897.8061

INACTIVE INGREDIENT

Inactive Ingredients Water (Aqua), Potassium Cocoate, Hexylene Glycol, Sodium Sulfate, Tetrasodium EDTA, Sodium lauryl sulfate, Hydroxyethylcellulose, Glycerin, Coco-glucoside, Glyceryl Oleate, fragrance, sodium glycolate, Sodium Hydroxide, Trisodium EDTA, Disodium EDTA, Sodium Citrate, Methylchloroisothiazolinone, Methylisothiazolinone, Red 40, Yellow 5, Red 33

Principal display panel and representative label

Member's Mark

COMMERCIAL

ANTIBACTERIAL

HAND SOAP

- KILLS 99.9% OF GERMS*
- FRESH, CLEAN FRAGRANCE
- TRICLOSAN FREE

NET CONTENTS 1 GALLON (3.78 L)

Ecolab 4050 Corporate Drive, Ste. 100

Grapevine, Texas 76051 USA - 866.999.7484

(c) 2020 Ecolab USA Inc. All rights reserved

DISTRIBUTED BY SAM'S WEST, INC.

BENTONVILLE, AR 72716